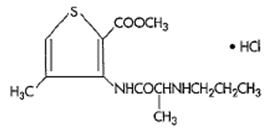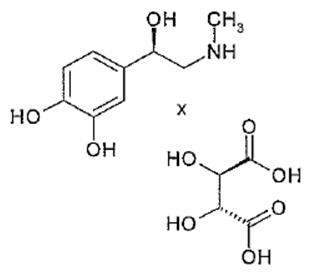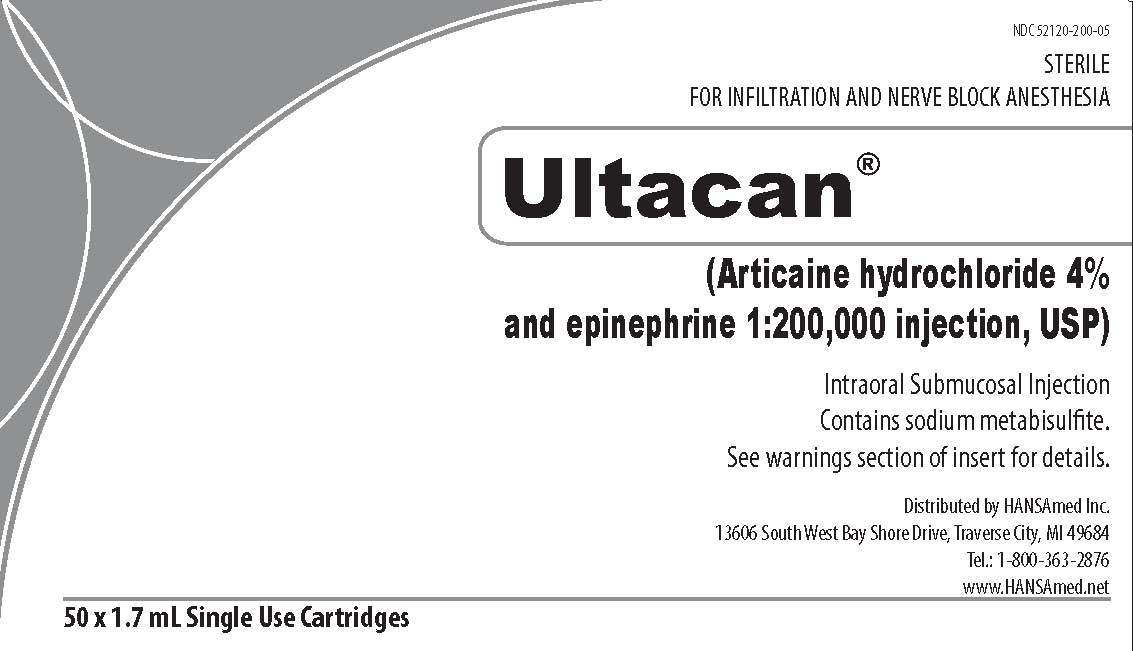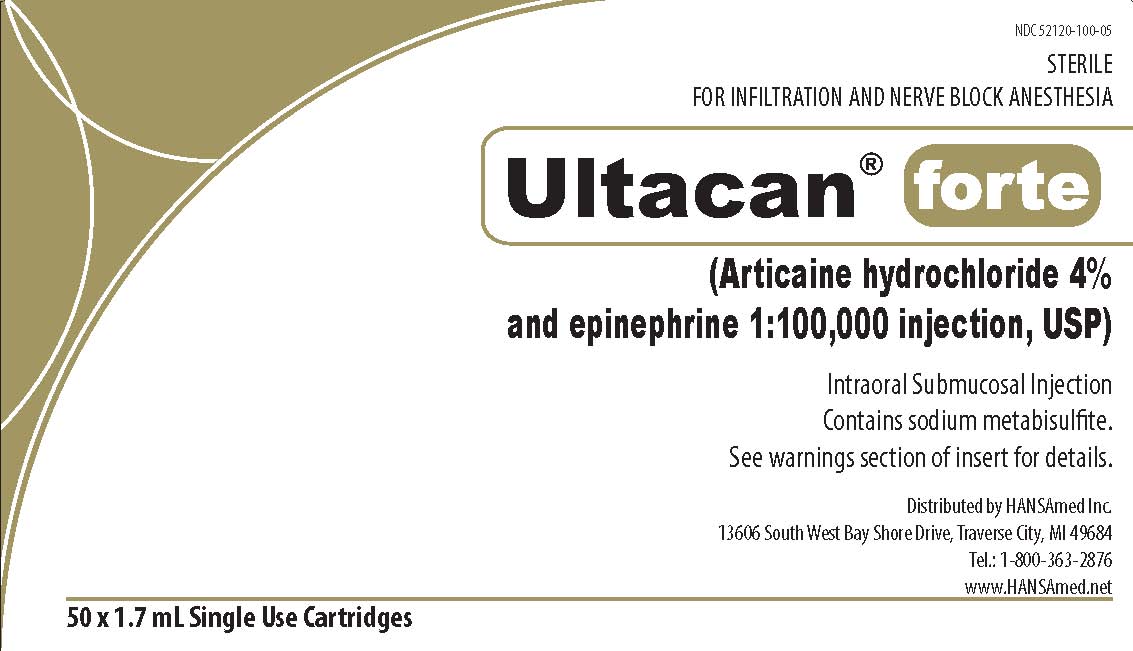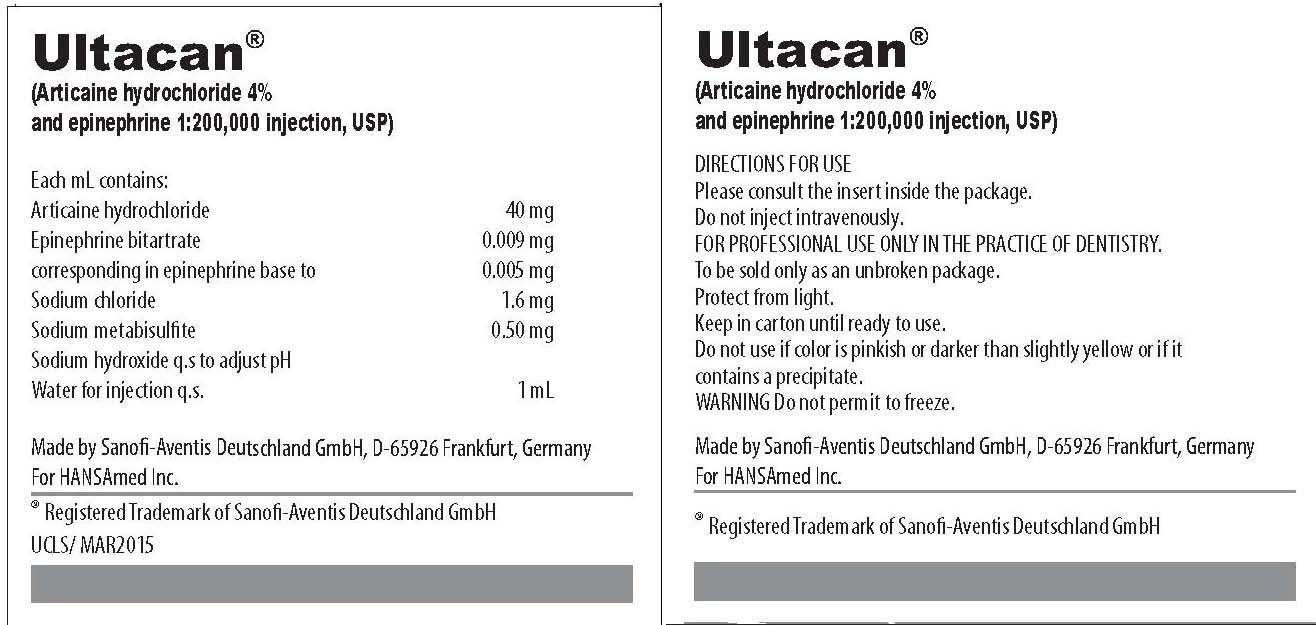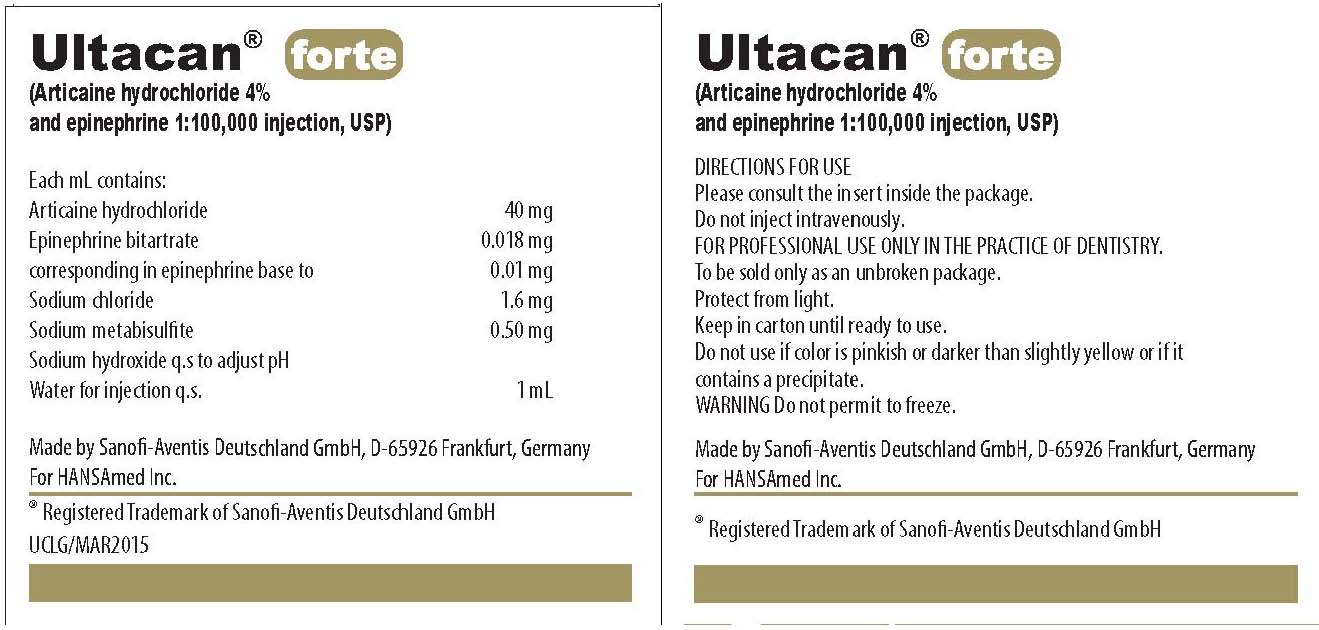 DRUG LABEL: Ultacan
NDC: 52120-200 | Form: INJECTION, SOLUTION
Manufacturer: HANSAmed, Inc.
Category: prescription | Type: HUMAN PRESCRIPTION DRUG LABEL
Date: 20170720

ACTIVE INGREDIENTS: ARTICAINE HYDROCHLORIDE 40 mg/1 mL; EPINEPHRINE BITARTRATE 0.009 mg/1 mL
INACTIVE INGREDIENTS: SODIUM CHLORIDE 1.6 mg/1 mL; SODIUM METABISULFITE 0.5 mg/1 mL; SODIUM HYDROXIDE

HIGHLIGHTS OF PRESCRIBING INFORMATION

These highlights do not include all the information needed to use Ultacan® and Ultacan® forte safely and effectively. See full prescribing information for Ultacan® and Ultacan® forte.
Ultacan® and Ultacan® forte (Articaine HCl 4% and epinephrine Injection, USP); Intraoral Submucosal Injection
Articaine hydrochloride 4% and epinephrine 1:200,000
Articaine hydrochloride 4% and epinephrine 1:100,000
Initial U.S. Approval: 2000

1 INDICATIONS AND USAGE

Ultacan® and Ultacan® forte, an amide local anesthetic containing a vasoconstrictor, are indicated for local, infiltrative, or conductive anesthesia in both simple and complex dental procedures.

2 DOSAGE AND ADMINISTRATION

For dental injection by submucosal infiltration or nerve block. (2.1)

- For infiltration: 0.5-2.5 mL (20-100 mg articaine HCl) (2.1)
- For nerve block: 0.5-3.4 mL (20-136 mg articaine HCl) (2.1)
- For oral surgery: 1.0-5.1 mL (40-204 mg articaine HCl) (2.1)
- For most routine dental procedures, Ultacan® containing epinephrine 1:200,000 is preferred. However, when more pronounced hemostasis or improved visualization of the surgical field are required, Ultacan® containing epinephrine 1:100,000 may be used. (2.1)
- Dosages should be reduced in pediatric patients, elderly patients, and patients with cardiac or liver disease. (2.1)

Maximum recommended dosages (2.2):

- Adults: 7 mg/kg (0.175 mL/kg)
- Children 4-16 years: 7 mg/kg (0.175 mL/kg), depending on the age, weight and magnitude of the operation.

3 DOSAGE FORMS AND STRENGTHS

Injection (clear colorless solution), containing:

- Articaine hydrochloride 4% (40 mg/mL) and epinephrine 1:200,000 (as epinephrine bitartrate 0.009 mg/mL) (3)
- Articaine hydrochloride 4% (40 mg/mL) and epinephrine 1:100,000 (as epinephrine bitartrate 0.018 mg/mL) (3)

4 CONTRAINDICATIONS

Known hypersensitivity to sulfite (4)

5 WARNINGS AND PRECAUTIONS

- Accidental Intravascular Injection: May be associated with convulsions followed by coma and respiratory arrest. Resuscitative equipment, oxygen and other resuscitative drugs should be available. (5.1)
- Systemic Toxicity (5.2)
- Vasoconstrictor Toxicity: Local anesthetic solutions like Ultacan® or Ultacan® forte that contain a vasoconstrictor should be used cautiously, especially in patients with impaired cardiovascular function or vascular disease. (5.3)
- Methemoglobinemia (5.4)
- Anaphylaxis and Allergic-Type Reactions (5.5)

6 ADVERSE REACTIONS

The most common adverse reactions (incidence >2%) are headache and pain. (6.1)
To report SUSPECTED ADVERSE REACTIONS, contact HANSAmed at 1-800-363-2876 or FDA at 1-800-FDA-1088 or www.fda.gov/medwatch

7 DRUG INTERACTIONS

- Monoamine oxidase inhibitors, nonselective beta adrenergic antagonists, or tricyclic antidepressants may produce severe, prolonged hypertension (7)
- Phenothiazines and butyrophenones may reduce or reverse the pressor effect of epinephrine (7)

8 USE IN SPECIFIC POPULATIONS

- Pregnancy: Based on animal studies, may cause fetal harm. (8.1)
- Nursing Mothers: Exercise caution when administering to a nursing woman. (8.3)
- Pediatric Use: Safety and effectiveness in pediatric patients below the age of 4 years have not been established. (8.4)

FULL PRESCRIBING INFORMATION

1 INDICATIONS AND USAGE

Ultacan® and Ultacan® forte, an amide local anesthetic containing a vasoconstrictor, are indicated for local, infiltrative, or conductive anesthesia in both simple and complex dental procedures.

2 DOSAGE AND ADMINISTRATION

2.1 General Dosing Information

Table 1 (below) summarizes the recommended volumes and concentrations of Ultacan® and Ultacan® forte for various types of anesthetic procedures. The dosages suggested in this table are for normal healthy adults, administered by submucosal infiltration or nerve block.

Table 1: Recommended Dosages for Both Strengths
Procedure | Ultacan® and Ultacan® forte Injection
Procedure | Volume (mL) | Total dose of articaine HCl (mg)
Infiltration | 0.5–2.5 | 20–100
Nerve block | 0.5–3.4 | 20–136
Oral surgery | 1.0–5.1 | 40–204

The recommended doses serve only as a guide to the amount of anesthetic required for most routine procedures. The actual volumes to be used depend on a number of factors such as type and extent of surgical procedure, depth of anesthesia, degree of muscular relaxation, and condition of the patient. In all cases, the smallest dose that will produce the desired result should be given.

The onset of anesthesia and the duration of anesthesia are proportional to the volume and concentration (i.e., total dose) of local anesthetic used. Caution should be exercised when employing large volumes because the incidence of side effects may be dose-related.

For most routine dental procedures, Ultacan® containing epinephrine 1:200,000 is preferred. However, when more pronounced hemostasis or improved visualization of the surgical field are required, Ultacan® forte containing epinephrine 1:100,000 may be used.

2.2 Maximum Recommended Dosages

- Adults: For normal healthy adults, the maximum dose of Articaine HCl 4% with epinephrine administered by submucosal infiltration or nerve block should not exceed 7 mg/kg (0.175 mL/kg).
- Pediatric Patients Ages 4 to 16 Years: The quantity of Articaine HCl 4% with epinephrine in children ages 4 to 16 years of age to be injected should be determined by the age and weight of the child and the magnitude of the operation. The maximum dose of Articaine HCl 4% with epinephrine should not exceed 7 mg/kg (0.175 mL/kg) [see Use in Specific Populations (8.4)].
- Safety and effectiveness of Articaine HCl 4% with epinephrine in pediatric patients below the age of 4 years have not been established.

2.3 Dosing in Special Populations

Dose reduction may be required in debilitated patients, acutely ill patients, elderly patients, and pediatric patients commensurate with their age and physical condition. No studies have been performed in patients with renal or liver dysfunction. Caution should be used in patients with severe liver disease. [see Warnings and Precautions (5.2), Use in Specific Populations (8.4, 8.5, and 8.6)]

3 DOSAGE FORMS AND STRENGTHS

Injection (clear colorless solution), containing:

- Articaine hydrochloride 4% (40 mg/mL) and epinephrine 1:200,000 (as epinephrine bitartrate 0.009 mg/mL)
- Articaine hydrochloride 4% (40 mg/mL) and epinephrine 1:100,000 (as epinephrine bitartrate 0.018 mg/mL)

4 CONTRAINDICATIONS

Ultacan® and Ultacan® forte are contraindicated in patients who are hypersensitive to products containing sulfites. Products containing sulfites may cause allergic-type reactions including anaphylactic symptoms and life-threatening or less severe asthmatic episodes in certain susceptible people. Sulfite sensitivity is seen more frequently in asthmatic than in non-asthmatic people [see Warnings and Precautions (5.5)].

5 WARNINGS AND PRECAUTIONS

5.1 Accidental Intravascular Injection

Accidental intravascular injection of Ultacan® or Ultacan® forte may be associated with convulsions, followed by central nervous system or cardiorespiratory depression and coma, progressing ultimately to respiratory arrest. Dental practitioners who employ local anesthetic agents including Ultacan® or Ultacan® forte should be well versed in diagnosis and management of emergencies that may arise from their use. Resuscitative equipment, oxygen, and other resuscitative drugs should be available for immediate use. To avoid intravascular injection, aspiration should be performed before Ultacan® or Ultacan® forte is injected. The needle must be repositioned until no return of blood can be elicited by aspiration. Note, however, that the absence of blood in the syringe does not guarantee that intravascular injection has been avoided.

Small doses of local anesthetics injected in dental blocks may produce adverse reactions similar to systemic toxicity seen with unintentional intravascular injections of larger doses. Confusion, convulsions, respiratory depression or respiratory arrest, and cardiovascular stimulation or depression have been reported. These reactions may be due to intra-arterial injection of the local anesthetic with retrograde flow to the cerebral circulation. Patients receiving these blocks should be observed constantly. Resuscitative equipment and personnel for treating adverse reactions should be immediately available. Dosage recommendations should not be exceeded [see Dosage and Administration (2.1)].

5.2 Systemic Toxicity

This includes toxicity arising from accidental intravascular injection of Ultacan® or Ultacan® forte discussed in Section 5.1, as well as that related to higher systemic concentrations of local anesthetics or epinephrine [see Warnings and Precautions (5.3)]. Systemic absorption of local anesthetics including Ultacan® or Ultacan® forte can produce effects on the central nervous and cardiovascular systems.

At blood concentrations achieved with therapeutic doses of Ultacan® or Ultacan® forte , changes in cardiac conduction, excitability, refractoriness, contractility, and peripheral vascular resistance are minimal. However, toxic blood concentrations of Ultacan® or Ultacan® forte can depress cardiac conduction and excitability, which may lead to atrioventricular block, ventricular arrhythmias, and cardiac arrest, possibly resulting in fatalities. In addition, myocardial contractility is depressed and peripheral vasodilatation occurs, leading to decreased cardiac output and arterial blood pressure. Ultacan® or Ultacan® forte should also be used with caution in patients with heart block as well as those with impaired cardiovascular function since they may be less able to compensate for functional changes associated with the prolongation of A-V conduction produced by these drugs.

Restlessness, anxiety, tinnitus, dizziness, blurred vision, tremors, depression, or drowsiness may be early warning signs of central nervous system toxicity.

Careful and constant monitoring of cardiovascular and respiratory (adequacy of ventilation) vital signs and the patient’s state of consciousness should be performed after each local anesthetic injection of Ultacan® or Ultacan® forte . Repeated doses of Ultacan® or Ultacan® forte may cause significant increases in blood levels because of possible accumulation of the drug or its metabolites. The lowest dosage that results in effective anesthesia should be used to decrease the risk of high plasma levels and serious adverse effects. Tolerance to elevated blood levels varies with the status of the patient. Resuscitative equipment, oxygen, and other resuscitative drugs should be available for immediate use. Precautions for epinephrine administration, discussed in Section 5.3, should be observed.

Debilitated patients, elderly patients, acutely ill patients, and pediatric patients should be given reduced doses commensurate with their age and physical condition [see Dosage and Administration (2.1, 2.3)]. No studies have been performed in patients with liver dysfunction, and caution should be used in patients with severe hepatic disease.

5.3 Vasoconstrictor Toxicity

Ultacan® and Ultacan® forte contain epinephrine, a vasoconstrictor that can cause local or systemic toxicity and should be used cautiously. Local toxicity may include ischemic injury or necrosis, which may be related to vascular spasm. Ultacan® and Ultacan® forte should be used with caution in patients during and following the administration of potent general anesthetic agents, since cardiac arrhythmias may occur under such conditions. Patients with peripheral vascular disease and those with hypertensive vascular disease may exhibit exaggerated vasoconstrictor response.

The American Heart Association has made the following recommendation regarding the use of local anesthetics with vasoconstrictors in patients with ischemic heart disease: “Vasoconstrictor agents should be used in local anesthesia solutions during dental practice only when it is clear that the procedure will be shortened or the analgesia rendered more profound. When a vasoconstrictor is indicated, extreme care should be taken to avoid intravascular injection. The minimum possible amount of vasoconstrictor should be used.” (Kaplan, 1986).

It is essential to aspirate before any injection to avoid administration of the drug into the blood stream.

5.4 Methemoglobinemia

Articaine, like other local anesthetics, can cause methemoglobinemia, particularly in conjunction with methemoglobin-inducing agents. Ultacan® and Ultacan® forte should not be used in patients with congenital or idiopathic methemoglobinemia, or in patients who are receiving treatment with methemoglobin-inducing agents since they are more susceptible to drug-induced methemoglobinemia.

Signs and symptoms of methemoglobinemia may be delayed some hours after exposure. Initial signs and symptoms of methemoglobinemia include slate grey cyanosis seen in buccal mucous membranes, lips, and nail beds. In severe cases, symptoms may include central cyanosis, headache, lethargy, dizziness, fatigue, syncope, dyspnea, CNS depression, seizures, dysrythmia, and shock. Methemoglobinemia should be considered if central cyanosis unresponsive to oxygen therapy occurs, especially if methemoglobin-inducing agents have been used. Calculated oxygen saturation and pulse oximetry are inaccurate in the setting of methemoglobinemia. The diagnosis can be confirmed by an elevated methemoglobin level of at least 10% is present. The development of methemoglobinemia is dose-related.

Management of methemoglobinemia: If methemoglobinemia does not respond to administration of oxygen, clinically significant symptoms of methemoglobinemia should be treated with administration of a slow intravenous injection (over 5 minutes) of methylene blue at a dosage of 1-2 mg/kg body weight.

5.5 Anaphylaxis and Allergic-Type Reactions

Ultacan® and Ultacan® forte contains sodium metabisulfite, a sulfite that may cause allergic-type reactions including anaphylactic symptoms and life-threatening or less severe asthmatic episodes in certain susceptible people. The overall prevalence of sulfite sensitivity in the general population is unknown. Sulfite sensitivity is seen more frequently in asthmatic than in non-asthmatic people.

6 ADVERSE REACTIONS

Reactions to articaine are characteristic of those associated with other amide-type local anesthetics. Adverse reactions to this group of drugs may also result from excessive plasma levels (which may be due to overdosage, unintentional intravascular injection, or slow metabolic degradation), injection technique, volume of injection, or hypersensitivity or they may be idiosyncratic.

6.1 Clinical Studies Experience

Because clinical trials are conducted under widely varying conditions, adverse reaction rates observed in the clinical trials of a drug cannot be directly compared to rates in the clinical trials of another drug and may not reflect the rates observed in practice.

The reported adverse reactions are derived from clinical trials in the United States and the United Kingdom. Table 2 displays the adverse reactions reported in clinical trials where 882 individuals were exposed to Articaine HCl 4% with epinephrine 1:100,000. Table 3 displays the adverse reactions reported in clinical trials where 182 individuals were exposed to Articaine HCl 4% with epinephrine 1:100,000 and 179 individuals were exposed to Articaine HCl 4% with epinephrine 1:200,000.

Adverse reactions observed in at least 1% of patients:

Table 2: Adverse Reactions in Controlled Trials with an Incidence of 1% or Greater in Patients Administered Articaine HCl 4%with Epinephrine 1:100,000
Body System/Reaction | Articaine HCl 4% with epinephrine 1:100,000 (N=882) Incidence
Body as a whole
Face Edema | 13 (1%)
Headache | 31 (4%)
Infection | 10 (1%)
Pain | 114 (13%)
Digestive system
Gingivitis | 13 (1%)
Nervous system
Paresthesia | 11 (1%)

Table 3: Adverse Reactions in Controlled Trials with an Incidence of 1% or Greater in Patients Administered Articaine HCl 4% with Epinephrine 1:200,000 and Articaine HCl 4% with Epinephrine 1:100,000
Reaction | Articaine HCl 4% with epinephrine 1:200,000 (N=179) Incidence | Articaine HCl 4% with epinephrine 1:100,000 (N=182) Incidence
Any adverse reaction | 33 (18%) | 35 (19%)
Pain | 11 (6.1%) | 14 (7.6%)
Headache | 9 (5%) | 6 (3.2%)
Positive blood aspiration into syringe | 3 (1.6%) | 6 (3.2%)
Swelling | 3 (1.6%) | 5 (2.7%)
Trismus | 1 (0.5%) | 3 (1.6%)
Nausea and emesis | 3 (1.6%) | 0 (0%)
Sleepiness | 2 (1.1%) | 1 (0.5%)
Numbness and tingling | 1 (0.5%) | 2 (1%)
Palpitation | 0 (0%) | 2 (1.%)
Ear symptoms (earache, otitis media) | 1 (0.5%) | 2 (1%)
Cough, persistent cough | 0 (0%) | 2 (1%)

Adverse reactions observed in less than 1% of patients:

Table 4: Adverse Reactions in Controlled Trials with an Incidence of Less than 1% but Considered Clinically Relevant in Patients Administered Articaine HCl 4% with epinephrine
Body System | Reactions
Body as a Whole | Asthenia; back pain; injection site pain; burning sensation above injection site; malaise; neck pain
Cardiovascular System | Hemorrhage; migraine; syncope; tachycardia; elevated blood pressure
Digestive System | Dyspepsia; glossitis; gum hemorrhage; mouth ulceration; nausea; stomatitis; tongue edemas; tooth disorder; vomiting
Hemic and Lymphatic System | Ecchymosis; lymphadenopathy
Metabolic and Nutritional System | Edema; thirst
Musculoskeletal System | Arthralgia; myalgia; osteomyelitis
Nervous System | Dizziness; dry mouth; facial paralysis; hyperesthesia; increased salivation; nervousness; neuropathy; paresthesia; somnolence; exacerbation of Kearns-Sayre Syndrome
Respiratory System | Pharyngitis; rhinitis; sinus pain; sinus congestion
Skin and Appendages | Pruritus; skin disorder
Special Senses | Ear pain; taste perversion

6.2 Postmarketing Experience

The following adverse reactions have been identified during postapproval use of Articaine HCl 4% with epinephrine. Because these reactions are reported voluntarily from a population of uncertain size, it is not always possible to reliably estimate their frequency or establish a casual relationship to drug exposure.

Persistent paresthesias of the lips, tongue, and oral tissues have been reported with use of articaine hydrochloride, with slow, incomplete, or no recovery. These postmarketing events have been reported chiefly following nerve blocks in the mandible and have involved the trigeminal nerve and its branches.

Hypoesthesia has been reported with use of articaine, especially in pediatric age groups, which is usually reversible. Prolonged numbness can result in soft tissue injuries such as that of the lips and tongue in these age groups.

Ischemic injury and necrosis have been described following use of articaine with epinephrine and have been postulated to be due to vascular spasm of terminal arterial branches.

Paralysis of ocular muscles has been reported, especially after posterior, superior alveolar injections of articaine during dental anesthesia. Symptoms include diplopia, mydriasis, ptosis and difficulty in abduction of the affected eye. These symptoms have been described as developing immediately after injection of the anesthetic solution and persisting one minute to several hours, with generally complete recovery.

7 DRUG INTERACTIONS

The administration of local anesthetic solutions containing epinephrine to patients receiving monoamine oxidase inhibitors, nonselective beta-adrenergic antagonists, or tricyclic antidepressants may produce severe, prolonged hypertension. Phenothiazines and butyrophenones may reduce or reverse the pressor effect of epinephrine. Concurrent use of these agents should be avoided; however, in situations when concurrent therapy is necessary, careful patient monitoring is essential [see Warnings and Precautions (5.1)].

8 USE IN SPECIFIC POPULATIONS

8.1 Pregnancy

Teratogenic Effects - Pregnancy Category C.

There are no adequate and well-controlled studies in pregnant women with Articaine HCl 4% with epinephrine. Articaine hydrochloride 4% and epinephrine (1:100,000) has been shown to increase fetal deaths and skeletal variations in rabbits when given in doses approximately 4 times the maximum recommended human dose (MRHD). Ultacan® or Ultacan® forte should be used during pregnancy only if the potential benefit justifies the potential risk to the fetus.

In embryo-fetal toxicity studies in rabbits, 80 mg/kg, subcutaneously (approximately 4 times the MRHD based on body surface area) caused fetal death and increased fetal skeletal variations, but these effects may be attributable to severe maternal toxicity, including seizures, observed at this dose. In contrast, no embryo-fetal toxicities were observed when articaine hydrochloride 4% and epinephrine (1:100,000) was administered subcutaneously throughout organogenesis at doses up to 40 mg/kg in rabbits and 80 mg/kg in rats (approximately 2 times the MRHD based on body surface area).

In pre- and postnatal developmental studies subcutaneous administration of articaine hydrochloride to pregnant rats throughout gestation and lactation, at a dose of 80 mg/kg (approximately 2 times the MRHD based on body surface area) increased the number of stillbirths and adversely affected passive avoidance, a measure of learning, in pups. This dose also produced severe maternal toxicity in some animals. A dose of 40 mg/kg (approximately equal to the MRHD on a mg/m2 basis) did not produce these effects. A similar study using articaine hydrochloride 4% and epinephrine (1:100,000) rather than articaine hydrochloride alone produced maternal toxicity, but no effects on offspring.

8.3 Nursing Mothers

It is not known whether Articaine HCl 4% with epinephrine is excreted in human milk. Because many drugs are excreted in human milk, caution should be exercised when Ultacan® or Ultacan® forte is administered to a nursing woman. When using Ultacan®or Ultacan® forte , nursing mothers may choose to pump and discard breast milk for approximately 4 hours (based on plasma half life) following an injection of Ultacan® or Ultacan® forte (to minimize infant ingestion) and then resume breastfeeding.

8.4 Pediatric Use

Safety and effectiveness of Articaine HCl 4% with epinephrine in pediatric patients below the age of 4 years have not been established. Safety of doses greater than 7 mg/kg (0.175 mL/kg) in pediatric patients has not been established. Safety and effectiveness was established in clinical trials with 61 pediatric patients between the ages of 4 and 16 years administered articaine hydrochloride 4% and epinephrine 1:100,000 injections. Fifty-one of these patients received doses from 0.76 mg/kg to 5.65 mg/kg (0.9 to

5.1 mL) for simple dental procedures and 10 patients received doses between 0.37 mg/kg and 7.48 mg/kg (0.7 to 3.9 mL) for complex dental procedures. Approximately 13% of these pediatric patients required additional injections of anesthetic for complete anesthesia. Dosages in pediatric patients should be reduced, commensurate with age, body weight, and physical condition [see Dosage and Administration (2.2)].

8.5 Geriatric Use

In clinical trials, 54 patients between the ages of 65 and 75 years, and 11 patients 75 years and over received Articaine HCl 4% with epinephrine 1:100,000. Among all patients between 65 and 75 years, doses from 0.43 mg/kg to 4.76 mg/kg (0.9 to 11.9 mL) were administered to 35 patients for simple procedures and doses from 1.05 mg/kg to 4.27 mg/kg (1.3 to 6.8 mL) were administered to 19 patients for complex procedures. Among the 11 patients = 75 years old, doses from 0.78 mg/kg to 4.76 mg/kg (1.3 to 11.9 mL) were administered to 7 patients for simple procedures and doses of 1.12 mg/kg to 2.17 mg/kg (1.3 to 5.1 mL) were administered to 4 patients for complex procedures.

Approximately 6% of patients between the ages of 65 and 75 years and none of the 11 patients 75 years of age or older required additional injections of anesthetic for complete anesthesia compared with 11% of patients between 17 and 65 years old who required additional injections.

No overall differences in safety or effectiveness were observed between elderly subjects and younger subjects, and other reported clinical experience has not identified differences in responses between the elderly and younger patients, but greater sensitivity of some older individuals cannot be ruled out.

8.6 Renal/Hepatic Insufficiency

No studies have been performed with articaine hydrochloride 4% and epinephrine 1:200,000 injection or articaine hydrochloride 4% and epinephrine 1:100,000 injection in patients with renal or hepatic dysfunction [see Warnings and Precautions (5.2)].

10 OVERDOSAGE

Acute emergencies from local anesthetics are generally related to high plasma levels encountered during therapeutic use of local anesthetics or to unintended subarachnoid injection of local anesthetic solution [see Warnings and Precautions (5.1, 5.2)].

The first consideration is prevention, best accomplished by careful and constant monitoring of cardiovascular and respiratory vital signs and the patient’s state of consciousness after each local anesthetic injection. At the first sign of change, oxygen should be administered.

The first step in the management of convulsions, as well as hypo-ventilation, consists of immediate attention to the maintenance of a patent airway and assisted or controlled ventilation as needed. The adequacy of the circulation should be assessed. Should convulsions persist despite adequate respiratory support, treatment with appropriate anticonvulsant therapy is indicated. The practitioner should be familiar with the use of anticonvulsant drugs, prior to the use of local anesthetics. Supportive treatment of circulatory depression may require administration of intravenous fluids and, when appropriate, a vasopressor.

If not treated immediately, both convulsions and cardiovascular depression can result in hypoxia, acidosis, bradycardia, arrhythmias, and/or cardiac arrest. If cardiac arrest should occur, standard cardiopulmonary resuscitative measures should be instituted.

For additional information about overdose treatment, call a poison control center (1-800-222-1222).

11 DESCRIPTION

Ultacan® and Ultacan® forte injection are a sterile, aqueous solution that contains articaine HCl 4% (40 mg/mL) and epinephrine bitartrate in an epinephrine 1:200,000 or epinephrine 1:100,000 strength. Articaine HCl is an amino amide local anesthetic, chemically designated as 4-methyl-3-[2-(propylamino)-propionamido]-2-thiophenecarboxylic acid, methyl ester hydrochloride and is a racemic mixture. Articaine HCl has a molecular weight of 320.84 and the following structural formula:

Articaine HCl has a partition coefficient in n-octanol/Soerensen buffer (pH 7.35) of 17 and a pKa of 7.8.

Epinephrine bitartrate, (-)-1-(3,4-Dihydroxyphenyl)-2-methylamino-ethanol (+) tartrate (1:1) salt, is a vasoconstrictor that is added to articaine HCl in a concentration of 1:200,000 or 1:100,000 (expressed as free base). It has a molecular weight of 333.3 and the following structural formula:

Ultacan® and Ultacan® forte contain articaine HCl (40 mg/mL), epinephrine (1:200,000 or 1:100,000) (as epinephrine bitartrate), sodium chloride (1.6 mg/mL), and sodium metabisulfite (0.5 mg/mL). The product is formulated with a 15% overage of epinephrine. The pH is adjusted with sodium hydroxide.

12 CLINICAL PHARMACOLOGY

12.1 Mechanism of Action

Articaine HCl is an amide local anesthetic. Local anesthetics block the generation and conduction of nerve impulses, presumably by increasing the threshold for electrical excitation in the nerve, by slowing the propagation of the nerve impulse, and by reducing the rate of rise of the action potential. In general, the progression of anesthesia is related to the diameter, myelination, and conduction velocity of the affected nerve fibers. Epinephrine is a vasoconstrictor added to articaine HCl to slow absorption into the general circulation and thus prolong maintenance of an active tissue concentration.

12.2 Pharmacodynamics

Clinically, the order of loss of nerve function is as follows: (1) pain; (2) temperature; (3) touch; (4) proprioception; and (5) skeletal muscle tone.

The onset of anesthesia has been shown to be within 1 to 9 minutes of injection of Articaine HCl 4% with epinephrine. Complete anesthesia lasts approximately 1 hour for infiltrations and up to approximately 2 hours for nerve block.

Administration of Articaine HCl 4% with epinephrine results in a 3-to 5-fold increase in plasma epinephrine concentrations compared to baseline; however, in healthy adults it does not appear to be associated with marked increases in blood pressure or heart rate, except in the case of accidental intravascular injection [see Warnings and Precautions (5.1)].

12.3 Pharmacokinetics

Absorption: Following dental injection by the submucosal route of an articaine solution containing epinephrine 1:200,000, articaine reaches peak blood concentration about 25 minutes after a single dose injection and 48 minutes after three doses. Peak plasma levels of articaine achieved after 68 and 204 mg doses are 385 and 900 ng/mL, respectively. Following intraoral administration of a near maximum dose of 476 mg, articaine reaches peak blood concentrations of 2037 and 2145 ng/mL for articaine solution containing epinephrine 1:100,000 and 1:200,000, respectively, approximately 22 minutes post-dose.

Distribution: Approximately 60 to 80% of articaine HCl is bound to human serum albumin and ?-globulins at 37°C in vitro.

Metabolism: Articaine HCl is metabolized by plasma carboxyesterase to its primary metabolite, articainic acid, which is inactive. In vitro studies show that the human liver microsome P450 isoenzyme system metabolizes approximately 5% to 10% of available articaine with nearly quantitative conversion to articainic acid.

Excretion: At the dose of 476 mg of articaine, the elimination half-life was 43.8 minutes and 44.4 minutes for articaine solution containing epinephrine 1:100,000 and 1:200,000, respectively. Articaine is excreted primarily through urine with 53-57% of the administered dose eliminated in the first 24 hours following submucosal administration. Articainic acid is the primary metabolite in urine. A minor metabolite, articainic acid glucuronide, is also excreted in urine. Articaine constitutes only 2% of the total dose excreted in urine.

Special Populations: No studies have been performed to evaluate the pharmacokinetics of Articaine HCl 4% with epinephrine injection in pediatric subjects. There is insufficient information to determine whether the pharmacokinetics of Articaine HCl 4% with epinephrine injection differs by race.

13 NONCLINICAL TOXICOLOGY

13.1 Carcinogenesis, Mutagenesis, Impairment of Fertility

Studies to evaluate the carcinogenic potential of articaine HCI in animals have not been conducted. Five standard mutagenicity tests, including three in vitro tests (the nonmammalian Ames test, the mammalian Chinese hamster ovary chromosomal aberration test, and a mammalian gene mutation test with articaine HCl) and two in vivo mouse micronucleus tests (one with articaine and epinephrine 1:100,000 and one with articaine HCl alone) showed no mutagenic effects.

No effects on male or female fertility were observed in rats for articaine hydrochloride 4% and epinephrine 1:100,000 administered subcutaneously in doses up to 80 mg/kg/day (approximately 2 times the MRHD based on body surface area).

14 CLINICAL STUDIES

Three randomized, double-blind, active-controlled studies were designed to evaluate effectiveness of Articaine HCl 4% containing epinephrine 1:100,000 as a dental anesthetic. Patients ranging in age from 4 years to over 65 years old underwent simple dental procedures such as single uncomplicated extractions, routine operative procedures, single apical resections, and single crown procedures, or complex dental procedures such as multiple extractions, multiple crowns and/or bridge procedures, multiple apical resections, alveolectomies, muco-gingival operations, and other surgical procedures on the bone. Articaine HCl 4% containing epinephrine 1:100,000 was administered as submucosal infiltration and/or nerve block. Efficacy was measured immediately following the procedure by having the patient and investigator rate the patient’s procedural pain using a 10 cm visual analog scale (VAS), in which a score of zero represented no pain and a score of 10 represented the worst pain imaginable. Mean patient and investigator VAS pain scores were 0.3-0.4 cm for simple procedures and 0.5-0.6 cm for complex procedures.

Four randomized, double-blind, active-controlled studies were performed comparing Articaine HCl 4% containing epinephrine 1:100,000 versus Articaine HCl 4% containing epinephrine 1:200,000. The first two studies used electric pulp testers (EPT) to evaluate the success rate (maximum EPT value within 10 minutes), onset, and duration of Articaine HCl 4% containing epinephrine 1:100,000 versus Articaine HCl 4% containing epinephrine 1:200,000 and articaine solution without epinephrine in healthy adults between 18 and 65 years old. Results indicated that the anesthetic characteristics of the 1:100,000 and 1:200,000 formulations are not significantly different.

A third study compared the difference in visualization of the surgical field after administration of Articaine HCl 4% containing epinephrine 1:100,000 versus Articaine HCl 4% containing epinephrine 1:200,000 during bilateral maxillary periodontal surgeries in patients ranging from 21 to 65 years old. Articaine HCl 4% containing epinephrine 1:100,000 provided better visualization of the surgical field and less blood loss during the procedures. In a fourth study, designed to assess and compare cardiovascular safety, when the maximum dose of each formulation was administered, no clinically relevant differences in blood pressure or heart rate between formulations were observed.

15 REFERENCES

Kaplan, EL, editor. Cardiovascular disease in dental practice. Dallas; American Heart Association; 1986.

16 HOW SUPPLIED/STORAGE AND HANDLING

Ultacan® and Ultacan® forte (articaine HCl 4% and epinephrine injection, USP) are available in 1.7 mL single use glass cartridges, packaged in boxes of 10 cartridges in the following two strengths:

- Ultacan® containing articaine HCl 4% (40 mg/mL) and epinephrine 1:200,000 (as epinephrine bitartrate 0.009 mg/mL) (NDC 52120-200-01)
- Ultacan® forte containing articaine HCl 4% (40 mg/mL) and epinephrine 1:100,000 (as epinephrine bitartrate 0.018 mg/mL) (NDC 52120-100-01)

Or, packaged in boxes of 50 cartridges in the following two strengths:

- Ultacan® containing articaine HCl 4% (40 mg/mL) and epinephrine 1:200,000 (as epinephrine bitartrate 0.009 mg/mL) (NDC 52120-200-05)
- Ultacan® forte containing articaine HCl 4% (40 mg/mL) and epinephrine 1:100,000 (as epinephrine bitartrate 0.018 mg/mL) (NDC 52120-100-05)

Or, packaged in boxes of 100 cartridges in the following two strengths:

- Ultacan® containing articaine HCl 4% (40 mg/mL) and epinephrine 1:200,000 (as epinephrine bitartrate 0.009 mg/mL) (NDC 52120-200-10)
- Ultacan® forte containing articaine HCl 4% (40 mg/mL) and epinephrine 1:100,000 (as epinephrine bitartrate 0.018 mg/mL) (NDC 52120-100-10)

Storage and Handling

Store at 20° to 25°C (68° to 77°F) [see USP Controlled Room Temperature]. Protect from light. Do Not Freeze.

For chemical disinfection of the carpule, either isopropyl alcohol (91%) or ethyl alcohol (70%) is recommended. Many commercially available brands of isopropyl (rubbing) alcohol, as well as solutions of ethyl alcohol not of U.S.P. grade, contain denaturants that are injurious to rubber and therefore are not to be used.

Parenteral drug products should be inspected visually for particulate matter and discoloration prior to administration, whenever solution and container permit.

17 PATIENT COUNSELING INFORMATION

Loss of Sensation and Muscle Function:

- Inform patients in advance of the possibility of temporary loss of sensation and muscle function following infiltration and nerve block injections [see Adverse Reactions (6.2)].
- Instruct patients not to eat or drink until normal sensation returns.

Manufactured for HANSAmed Inc. Traverse City, MI 49685

by Sanofi-Aventis Deutschland GmbH 65929 Frankfurt am Main, Germany

PRINCIPAL DISPLAY PANEL-1:200,000 Carton

Carton - Main 1:200,000

1:200,000 Carton Main

NDC 52120-200-05

Sterile
For Infiltration and Nerve Block Anesthesia

Ultacan®

(Articaine hydrochloride 4%
and epinephrine 1:200,000 injection, USP)

Intraoral Submucosal Injection
Contains sodium metabisulfite.
See warnings section of insert for details.

Distributed by HANSAmed Inc.
13606 South West Bay Shore Drive, Traverse City, MI 49684
Tel.: 1-800-363-2876
www.HANSAmed.net

50 × 1.7 mL Single Use Cartridges

PRINCIPAL DISPLAY PANEL-1:200,000 Carton Sides

Carton - Sides 1:200,000

1:200,000 Carton Right Side

Ultacan®

(Articaine hydrochloride 4%
and epinephrine 1:200,000 injection, USP)

DIRECTIONS FOR USE
Please consult the insert inside the package.
Do not inject intravenously.
FOR PROFESSIONAL USE ONLY IN THE PRACTICE OF DENTISTRY.
To be sold only as an unbroken package.
Protect from light.
Keep in carton until ready to use.
Do not use if color is pinkish or darker than slightly yellow or if it
contains a precipitate.
WARNING Do not permit to freeze.

Made by Sanofi-Aventis Deutschland GmbH, D-65926 Frankfurt, Germany
for HANSAmed Inc.

®Reg. Trademark of Sanofi-Aventis Deutschland GmbH

1:200,000 Carton Left Side

Ultacan®

(Articaine hydrochloride 4%
and epinephrine 1:200,000 injection, USP)

Each mL contains:
Articaine hydrochloride 40 mg
Epinephrine bitartrate 0.009 mg
corresponding in epinephrine base to 0.005 mg
Sodium chloride 1.6 mg
Sodium metabisulfite 0.50 mg
Sodium hydroxide q.s. to adjust pH
Water for injection q.s. 1 mL

Made by Sanofi-Aventis Deutschland GmbH, D-65926 Frankfurt, Germany
for HANSAmed Inc.

®Reg. Trademark of Sanofi-Aventis Deutschland GmbH

UCLS/MAR2015

PRINCIPAL DISPLAY PANEL-1:100,000 Carton

Carton - Main 1:100,000

1:100,000 Carton Main

NDC 52120-100-05

Sterile
For Infiltration and Nerve Block Anesthesia

Ultacan® forte

(Articaine hydrochloride 4%
and epinephrine 1:100,000 injection, USP)

Intraoral Submucosal Injection
Contains sodium metabisulfite
see warnings section of insert for details.

HANSAmed Inc.
13606 South West Bay Shore Drive, Traverse City, MI 49684
Tel.: 1-800-363-2876
www.HANSAmed.net

50 × 1.7 mL Single Use Cartridges

PRINCIPAL DISPLAY PANEL-1:100,000 Carton Sides

Carton - Sides 1:100,000

1:100,000 Carton Right Side

Ultacan® forte

(Articaine hydrochloride 4%
and epinephrine 1:100,000 injection, USP)

DIRECTIONS FOR USE
Please consult the insert inside the package.
Do not inject intravenously.
FOR PROFESSIONAL USE ONLY IN THE PRACTICE OF DENTISTRY.
To be sold only as an unbroken package.
Protect from light.
Keep in carton until ready to use.
Do not use if color is pinkish or darker than slightly yellow or if it
contains a precipitate.
WARNING Do not permit to freeze.

Made by Sanofi-Aventis Deutschland GmbH, D-65926 Frankfurt, Germany
for HANSAmed Inc.

®Reg. Trademark of Sanofi-Aventis Deutschland GmbH

1:100,000 Carton Left Side

Ultacan® forte

(Articaine hydrochloride 4%
and epinephrine 1:100,000 injection, USP)

Each mL contains:
Articaine hydrochloride 40 mg
Epinephrine bitartrate 0.018 mg
corresponding in epinephrine base to 0.01 mg
Sodium chloride 1.6 mg
Sodium metabisulfite 0.50 mg
Sodium hydroxide q.s. to adjust pH
Water for injection q.s. 1 mL

Made by Sanofi-Aventis Deutschland GmbH, D-65926 Frankfurt, Germany
for HANSAmed Inc.

®Reg. Trademark of Sanofi-Aventis Deutschland GmbH

UCLG/MAR2015